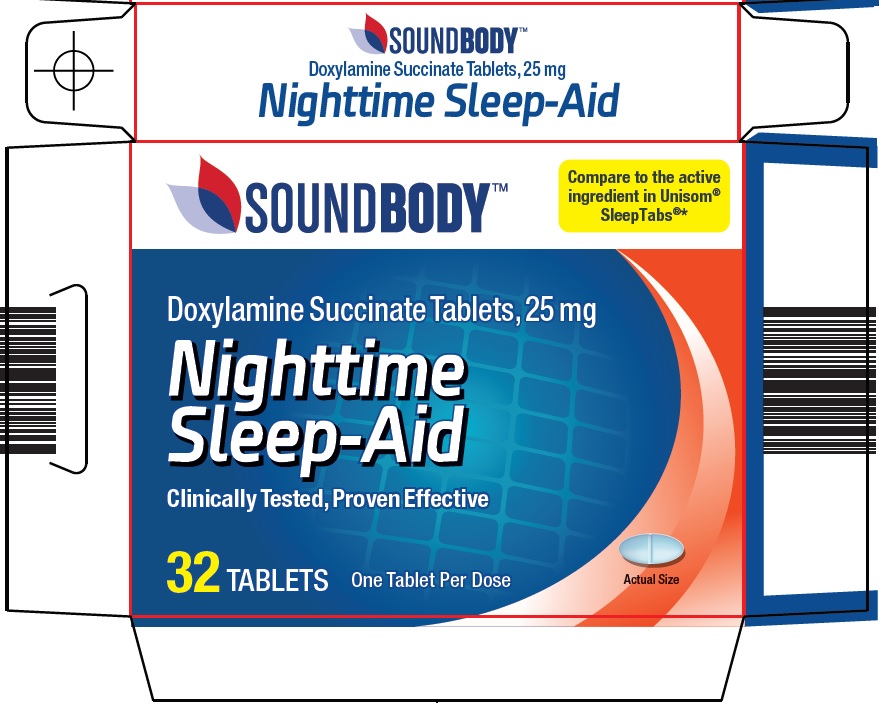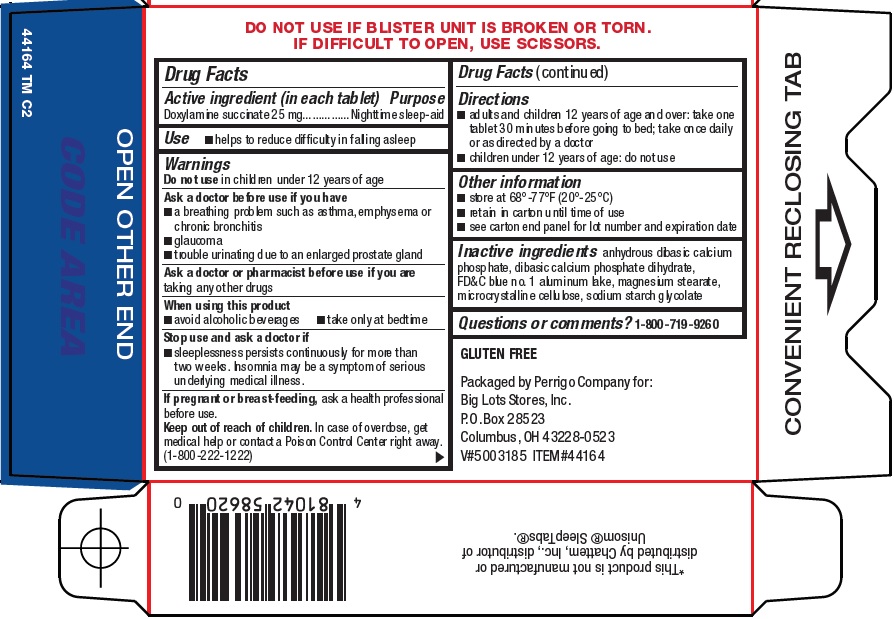 DRUG LABEL: sound body nighttime sleep aid
NDC: 50594-441 | Form: TABLET
Manufacturer: Big Lots Stores, Inc.
Category: otc | Type: HUMAN OTC DRUG LABEL
Date: 20200730

ACTIVE INGREDIENTS: DOXYLAMINE SUCCINATE 25 mg/1 1
INACTIVE INGREDIENTS: MAGNESIUM STEARATE; MICROCRYSTALLINE CELLULOSE; ANHYDROUS DIBASIC CALCIUM PHOSPHATE; DIBASIC CALCIUM PHOSPHATE DIHYDRATE; FD&C BLUE NO. 1

Big Lots, Inc Nighttime Sleep-Aid Drug Facts

Active ingredient (in each tablet)

Doxylamine succinate 25 mg

Purpose

Nighttime sleep-aid

Use

- helps to reduce difficulty in falling asleep

Warnings

Do not use

in children under 12 years of age

Ask a doctor before use if you have

- a breathing problem such as asthma, emphysema or chronic bronchitis
- glaucoma
- trouble urinating due to an enlarged prostate gland

Ask a doctor or pharmacist before use if you are

taking any other drugs

When using this product

- avoid alcoholic beverages
- take only at bedtime

Stop use and ask a doctor if

- sleeplessness persists continuously for more than two weeks. Insomnia may be a symptom of serious underlying medical illness.

If pregnant or breast-feeding,

ask a health professional before use.

Keep out of reach of children.

In case of overdose, get medical help or contact a Poison Control Center right away. (1-800-222-1222)

Directions

- adults and children 12 years of age and over: take one tablet 30 minutes before going to bed; take once daily or as directed by a doctor
- children under 12 years of age: do not use

Other information

- store at 68°-77°F (20°-25°C)
- retain in carton until time of use
- see carton end panel for lot number and expiration date

Inactive ingredients

anhydrous dibasic calcium phosphate, dibasic calcium phosphate dihydrate, FD&C blue no. 1 aluminum lake, magnesium stearate, microcrystalline cellulose, sodium starch glycolate

Questions or comments?

1-800-719-9260

Principal Display Panel

Compare to the active ingredient in Unisom® SleepTabs®

Doxylamine Succinate Tablets, 25 mg

Nighttime Sleep-Aid

Clinically Tested, Proven Effective

32 TABLETS

One Tablet Per Dose

Actual Size